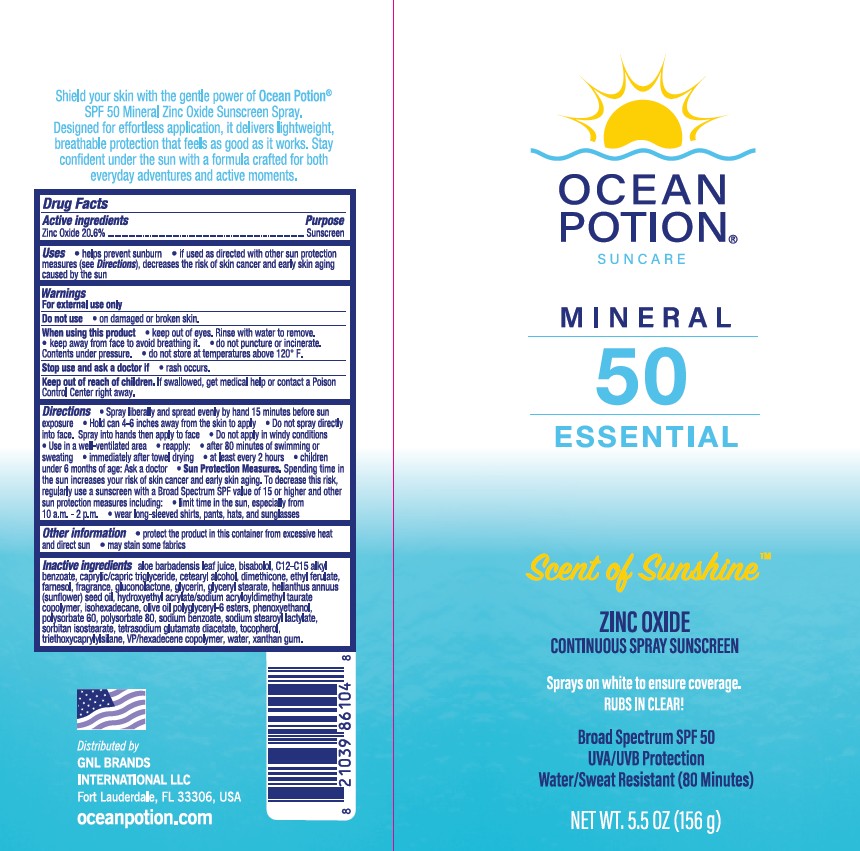 DRUG LABEL: Ocean Potion Suncare Mineral 50 Essential Scent of Sunshine Zinc Oxide Continuous Sunscreen
NDC: 85638-008 | Form: SPRAY
Manufacturer: GNL BRANDS INTERNATIONAL, LLC
Category: otc | Type: HUMAN OTC DRUG LABEL
Date: 20250818

ACTIVE INGREDIENTS: ZINC OXIDE 206 mg/1 g
INACTIVE INGREDIENTS: SODIUM BENZOATE; CETOSTEARYL ALCOHOL; HEXAMETHYLDISILOXANE; SUNFLOWER OIL; HYDROXYETHYL ACRYLATE/SODIUM ACRYLOYLDIMETHYL TAURATE COPOLYMER (100000 MPA.S AT 1.5%); LEVOMENOL; POLYSORBATE 60; FARNESOL; PHENOXYETHANOL; OLIVE OIL POLYGLYCERYL-6 ESTERS; SODIUM STEAROYL LACTYLATE; TETRASODIUM GLUTAMATE DIACETATE; WATER; ISOHEXADECANE; ALKYL (C12-15) BENZOATE; MEDIUM-CHAIN TRIGLYCERIDES; VINYLPYRROLIDONE/HEXADECENE COPOLYMER; SORBITAN ISOSTEARATE; ETHYL FERULATE; TRIETHOXYCAPRYLYLSILANE; GLUCONOLACTONE; POLYSORBATE 80; GLYCERYL MONOSTEARATE; .ALPHA.-TOCOPHEROL, DL-; ALOE VERA LEAF; GLYCERIN; XANTHAN GUM

Ocean Potion Suncare Mineral 50 Essential Scent of Sunshine Zinc Oxide Continuous Spray Sunscreen

Active ingredients

Zinc Oxide 20.6%

Purpose

Sunscreen

Uses

- helps prevent sunburn
- if used as directed with other sun protection measures (see Directions), decreases the risk of skin cancer and early skin aging caused by the sun

Warnings

For external use only

FLAMMABLE:

• do not use near heat, flame or while smoking
• avoid long term storage above 104°F (40°C)

Do not use

- on damaged or broken skin

When using this product

• keep out of eyes. Rinse with water to remove.

• keep away from to avoid breathing it.

• do not puncture or incinerate. Contents under pressure.

• do not store at temperatures above 120° F.

Stop use and ask doctor if

- rash occurs.

Keep out of reach of children.

If product is swallowed, get medical help or contact a Poison Control Center right away.

Directions

• spray liberally and spread evenly by hand 15 minutes before sun exposure
• hold can 4-6 inches away from skin top apply
• do not spray into face. Spray into hand and apply to face.
• use in a well ventilated areas
reapply:
• after 80 minutes of swimming or sweating
• immediately after towel drying
• at least every 2 hours

• children under 6 months: Ask a doctor
• Sun Protection Measures. Spending time in the sun increases your risk of skin cancer and early skin aging. To decrease this risk, regularly use a sunscreen with a Broad Spectrum SPF Value of 15 or higher and other sun protection measures including:
• limit time in the sun, especially from 10 a.m. - 2 p.m.
• wear long-sleeved shirts, pants, hats, and sunglasses

Other Information

• protect the product in the container from excessive heat and direct sun
• may stain or damage some fabrics

Inactive ingredients

aloe barbadensis leaf juice, bisabolol,
C12-C15 alkyl benzoate, caprylic/capric triglyceride, cetearyl alcohol,
dimethicone, ethyl ferulate, farnesol, fragrance, gluconolactone, glycerin, glyceryl
stearate, helianthus annuus (sunflower) seed oil, hydroxyethyl
acrylate/sodium acryloyldimethyl taurate copolymer, isohexadecane, olive
oil polyglyceryl-6 esters, phenoxyethanol, polysorbate 60, polysorbate 80,
sodium benzoate, sodium stearoyl lactylate, sorbitan isostearate,
tetrasodium glutamate diacetate, tocopherol, triethoxycaprylylsilane,
VP/hexadecene copolymer, water, xanthan gum